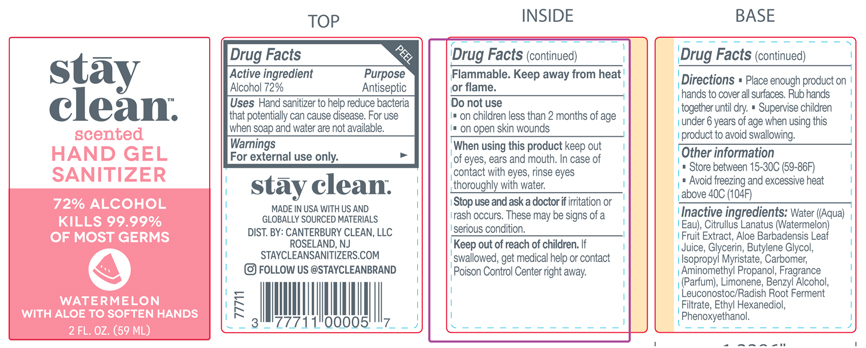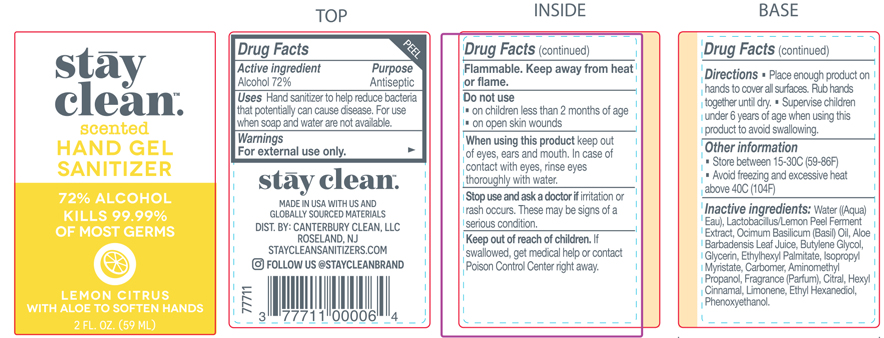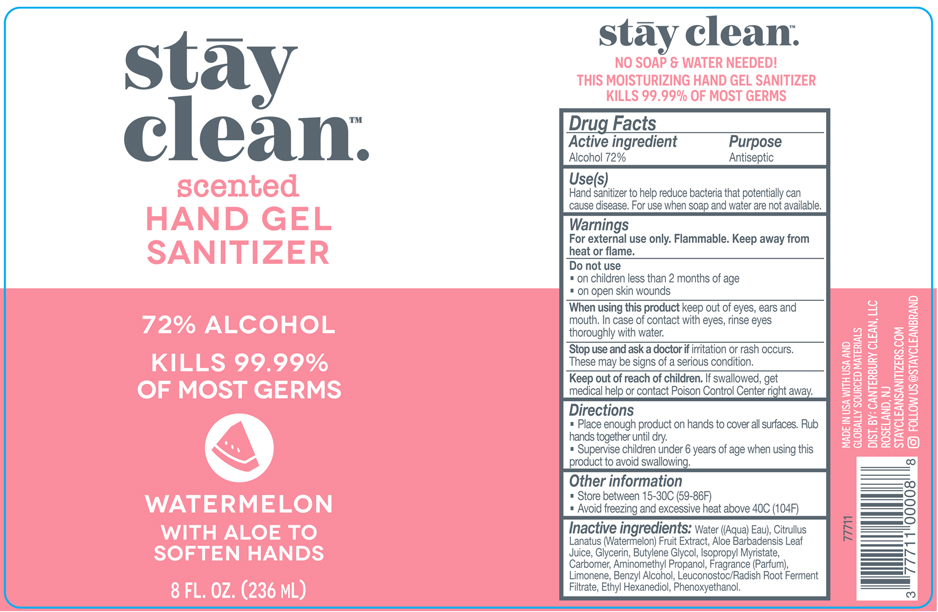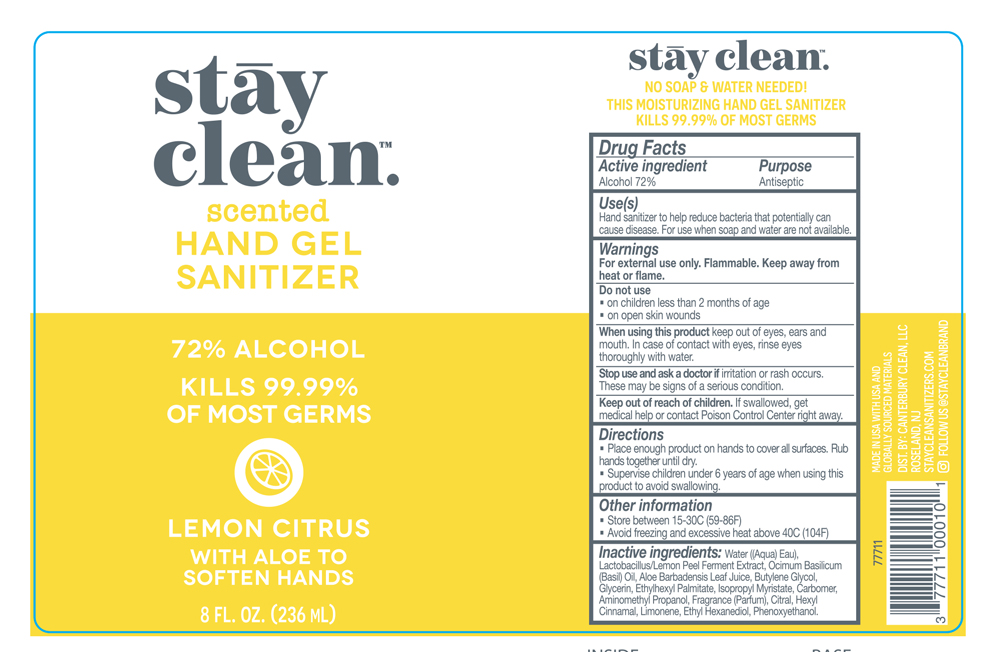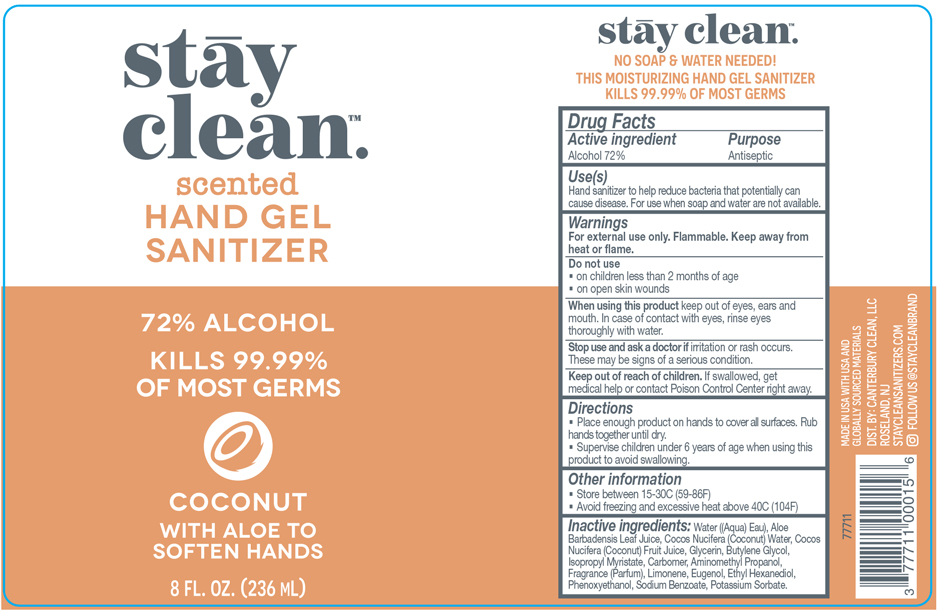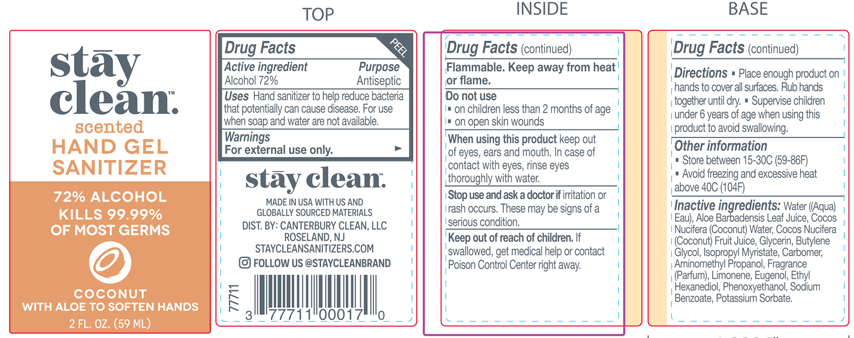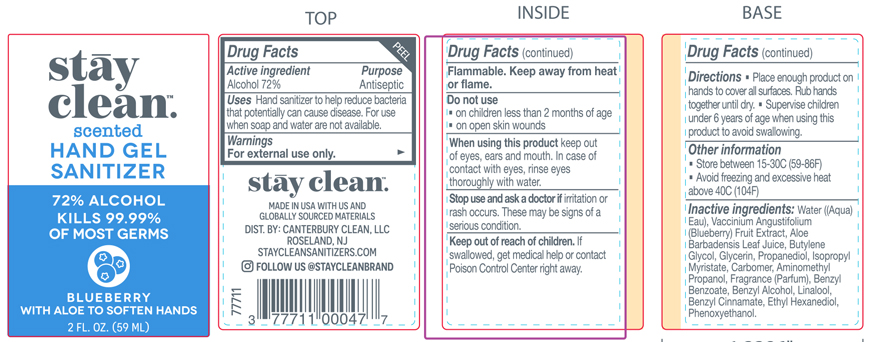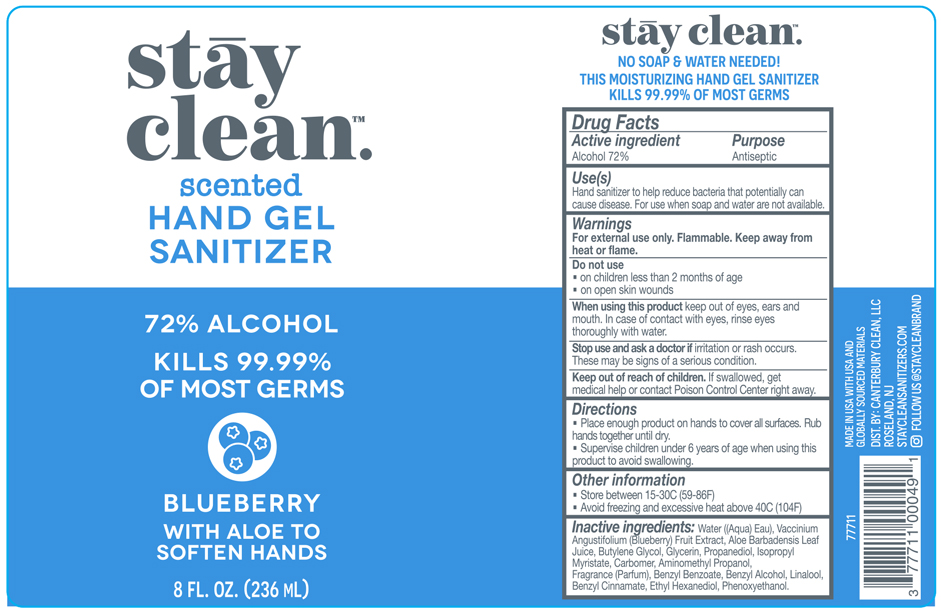 DRUG LABEL: StayClean Scented Hand Gel Sanitizer Blueberry 8 FL.OZ
NDC: 77711-005 | Form: GEL
Manufacturer: Canterbury Clean, LLC
Category: otc | Type: HUMAN OTC DRUG LABEL
Date: 20200813

ACTIVE INGREDIENTS: ALCOHOL 72 mL/100 mL
INACTIVE INGREDIENTS: LINALOOL, (+/-)- 0.00352 mL/100 mL; PROPANEDIOL 0.0095 mL/100 mL; BENZYL CINNAMATE 0.00122 mL/100 mL; ISOPROPYL MYRISTATE 0.001 mL/100 mL; LOWBUSH BLUEBERRY 0.0005 mL/100 mL; GLYCERIN 0.01 mL/100 mL; WATER 27.44597 mL/100 mL; AMINOMETHYLPROPANOL 0.06303 mL/100 mL; ALOE VERA LEAF 0.0098 mL/100 mL; ETHOHEXADIOL 0.00015 mL/100 mL; CARBOMER HOMOPOLYMER, UNSPECIFIED TYPE 0.25 mL/100 mL; BENZYL BENZOATE 0.10132 mL/100 mL; PHENOXYETHANOL 0.00005 mL/100 mL; BENZYL ALCOHOL 0.01306 mL/100 mL; BUTYLENE GLYCOL 0.01 mL/100 mL

This is a hand sanitizer manufactured according to the Temporary Policy for Preparation of Certain Alcohol-Based Hand Sanitizer Products During the Public Health Emergency (CoViD-19); Guidance for Industry.

The hand sanitizer is manufactured using only the following United States Pharmacopoeia (USP) grade ingredients in the preparation of the product (percentage in final product formulation) consistent with World Health Organization (WHO) recommendations:

1. Alcohol (ethanol) (USP or Food Chemical Codex (FCC) grade) (80%, volume/volume (v/v)) in an aqueous solution denatured according to Alcohol and Tobacco Tax and Trade Bureau regulations in 27 CFR part 20.
2. Glycerol (1.45% v/v).
3. Hydrogen peroxide (0.125% v/v).
4. Sterile distilled water or boiled cold water.

The firm does not add other active or inactive ingredients. Different or additional ingredients may impact the quality and potency of the product.

Active Ingredient(s)

Alcohol 72% v/v. Purpose: Antiseptic

Purpose

Antiseptic, Hand Sanitizer

Use

Hand Sanitizer to help reduce bacteria that potentially can cause disease. For use when soap and water are not available.

Warnings

For external use only. Flammable. Keep away from heat or flame

Do not use

- in children less than 2 months of age
- on open skin wounds

When using this product keep out of eyes, ears, and mouth. In case of contact with eyes, rinse eyes thoroughly with water.
Stop use and ask a doctor if irritation or rash occurs. These may be signs of a serious condition.
Keep out of reach of children. If swallowed, get medical help or contact a Poison Control Center right away.

Stop use and ask a doctor if irritation or rash occurs. These may be signs of a serious condition.

Keep out of reach of children. If swallowed, get medical help or contact a Poison Control Center right away.

Directions

- Place enough product on hands to cover all surfaces. Rub hands together until dry.
- Supervise children under 6 years of age when using this product to avoid swallowing.

Other information

- Store between 15-30C (59-86F)
- Avoid freezing and excessive heat above 40C (104F)

Inactive ingredients-Blue Berry 2 FL.OZ

Water, Carbomer, Benzyl Benzoate, Fragrance(Parfum), Aminomethyl Propanol,Benzyl Alcohol, Butylene Glycol, Glycerin, Aloe Barbadensis Leaf Juice, Propanediol, Linalool, Benzyl Cinnamate, Isopropyl Myristate, Vaccinium Angustifolium (Blueberry) Fruit Extract, Ethyl Hexanediol, Phenoxyethanol

Inactive Ingredient-Blue Berry 8 FL.OZ

Water, Carbomer, Benzyl Benzoate, Fragrance(Parfum), Aminomethyl Propanol,Benzyl Alcohol, Butylene Glycol, Glycerin, Aloe Barbadensis Leaf Juice, Propanediol, Linalool, Benzyl Cinnamate, Isopropyl Myristate, Vaccinium Angustifolium (Blueberry) Fruit Extract, Ethyl Hexanediol, Phenoxyethanol

Inactive Ingredient-Watermelon 2 FL.OZ

Water, Carbomer, Fragrance(Parfum), Aminomethyl Propanol,Glycerin, Butylene Glycol,Aloe Barbadensis Leaf Juice,Limonene, Benzyl Alcohol,Citrullus Lanatus (Watermelon) Fruit Extract, Isopropyl Myristate, Leuconostoc/Radish Root Ferment Filtrate, Ethyl Hexanediol, Phenoxyethanol

Inactive Ingredient-Watermelon 8 FL.OZ

Water, Carbomer, Fragrance(Parfum), Aminomethyl Propanol,Glycerin, Butylene Glycol,Aloe Barbadensis Leaf Juice,Limonene, Benzyl Alcohol,Citrullus Lanatus (Watermelon) Fruit Extract, Isopropyl Myristate, Leuconostoc/Radish Root Ferment Filtrate, Ethyl Hexanediol, Phenoxyethanol

Inactive Ingredeint-Lemon Citrus 2 FL.OZ

Water, Carbomer, Fragrance(Parfum),Limonene, Aminomethyl Propanol, Citral, Hexyl Cinnamal, Butylene Glycol, Glycerin, Aloe Barbadensis Leaf Juice, Ethylhexyl Palmitate, Lactobacillus/Lemon Peel Ferment Extract, Isopropyl Myristate, Ocimum Basilicum (Basil) Oil, Ethyl Hexanediol, Phenoxyethanol

Inactive Ingredient-Lemon Citrus 8 FL.OZ

Water, Carbomer, Fragrance(Parfum),Limonene, Aminomethyl Propanol, Citral, Hexyl Cinnamal, Butylene Glycol, Glycerin, Aloe Barbadensis Leaf Juice, Ethylhexyl Palmitate, Lactobacillus/Lemon Peel Ferment Extract, Isopropyl Myristate, Ocimum Basilicum (Basil) Oil, Ethyl Hexanediol, Phenoxyethanol

Inactive Ingredient-Coconut 2 FL.OZ

Water, Carbomer, Fragrance(Parfum),Aminomethyl Propanol, Glycerin, Limonene, Butylene Glycol, Aloe Barbadensis Leaf Juice, Cocos Nucifera (Coconut) Water, Eugenol, Isopropyl Myristate, Cocos Nucifera (Coconut) Fruit Juice, Ethyl Hexanediol, Phenoxyethanol, Sodium Benzoate, Potassium Sorbate

Inactive ingredeint-Coconut 8 FL.OZ

Water, Carbomer, Fragrance(Parfum),Aminomethyl Propanol, Glycerin, Limonene, Butylene Glycol, Aloe Barbadensis Leaf Juice, Cocos Nucifera (Coconut) Water, Eugenol, Isopropyl Myristate, Cocos Nucifera (Coconut) Fruit Juice, Ethyl Hexanediol, Phenoxyethanol, Sodium Benzoate, Potassium Sorbate

Package Label - Principal Display Panel-Blue Berry 2 FL.OZ

59 mL NDC: 77711-004-00

Package Label. Principal Display Panel-Blueberry 8 FL.OZ

236ml NDC:77711-005-00

Package Label. Principal Display Panel-Watermelon 2 FL.OZ

59ml NDC: 77711-006-00

Package Label. Principal Display Panel-Watermelon 8 FL.OZ

236ml, NDC: 77711-007-00

Package Label. Principal Display Panel-Lemon Citrus 2 FL.OZ

59ml NDC:77711-008-00

Package Label. Principal Display Panel-Lemon Citrus 8 FL.OZ

236ml NDC:77711-009-00

Package Label. Principal Display Panel-Coconut 2 FL.OZ

59 ml, NDC:77711-010-00

Package Label. Principal Display Panel-Coconut 8 FL.OZ

236ml NDC:77711-011-00